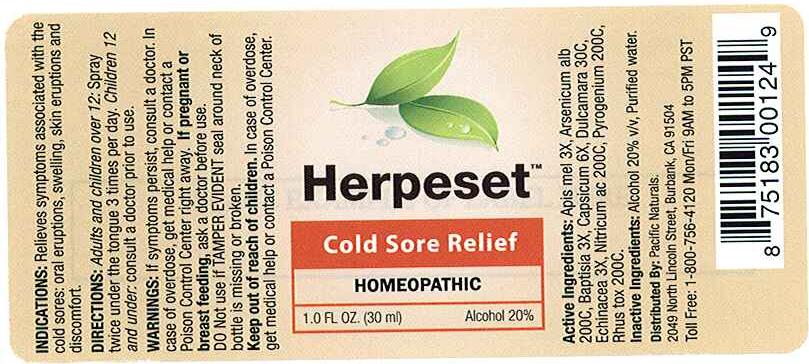 DRUG LABEL: Herpeset
NDC: 50845-0126 | Form: SPRAY
Manufacturer: Liddell Laboratories, Inc.
Category: homeopathic | Type: HUMAN OTC DRUG LABEL
Date: 20110707

ACTIVE INGREDIENTS: APIS MELLIFERA 3 [hp_X]/1 mL; ARSENIC TRIOXIDE 200 [hp_M]/1 mL; BAPTISIA TINCTORIA ROOT 3 [hp_X]/1 mL; CAPSICUM 6 [hp_X]/1 mL; SOLANUM DULCAMARA FLOWER 30 [hp_C]/1 mL; ECHINACEA 3 [hp_X]/1 mL; NITRIC ACID 200 [hp_C]/1 mL; RANCID BEEF 200 [hp_C]/1 mL; TOXICODENDRON PUBESCENS LEAF 200 [hp_C]/1 mL
INACTIVE INGREDIENTS: WATER; ALCOHOL

Herpeset

ACTIVE INGREDIENT

ACTIVE INGREDIENTS: Apis mellifica 3X, Arsenicum album 200C, Baptisia Tinctoria 3X, Capsicum annuum 6X, Dulcamara 30C, Echinacea 3X, Nitricum acidum 200C, Pyrogenium 200C, Rhus toxicodendron 200C.

PURPOSE

INDICATIONS: Relieves symptoms associated with the cold sores: oral eruptions, swelling, skin eruptions and discomfort.

WARNINGS: If symptoms persist, consult a doctor.

In case of overdose, get medical help or contact a Poison Control Center right away.

If pregnant or breast feeding, ask a doctor before use.

Do not use if TAMPER EVIDENT seal around neck of bottle is missing or broken.

Keep out of reach of children. In case of overdose, get medical help or contact a Poison Control Center.

DOSAGE AND ADMINISTRATION

DIRECTIONS: Adults and children over 12: Spray twice under the tongue 3 times per day

Children 12 and under: consult a doctor prior to use.

INACTIVE INGREDIENTS: Alcohol 20% v/v, Purified water.

KEEP OUT OF REACH OF CHILDREN. In case of overdose, get medical help or contact a Poison Control Center.

INDICATIONS AND USAGE

INDICATIONS: Relieves symptoms associated with the cold sores: oral eruptions, swelling, skin eruptions and discomfort.

QUESTIONS

Distributed By:

Pacific Naturals

2049 North Lincoln Street

Burbank, CA 91504

Toll Free: 1-800-756-4120 Mon/Fri 9AM to 5PM PST

PACKAGE LABEL

Herpeset

Cold Sore Relief

HOMEOPATHIC

1.0 FL OZ (30 ml)